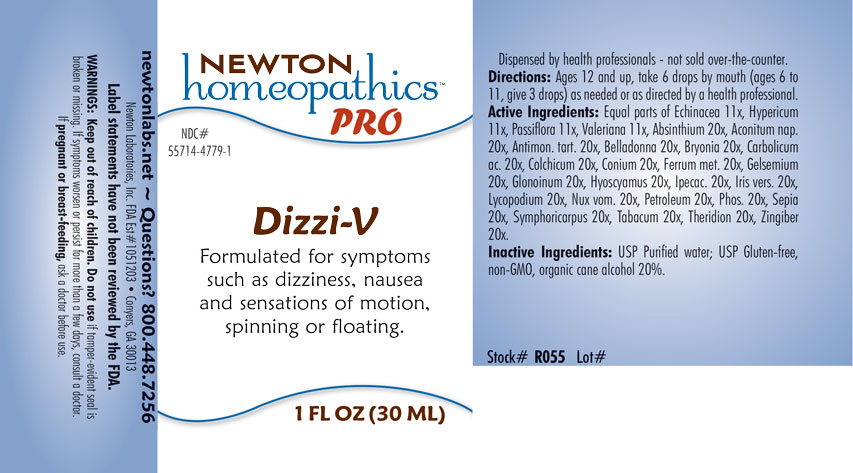 DRUG LABEL: Dizzi-V
NDC: 55714-4779 | Form: LIQUID
Manufacturer: Newton Laboratories, Inc.
Category: homeopathic | Type: HUMAN OTC DRUG LABEL
Date: 20201202

ACTIVE INGREDIENTS: WORMWOOD 20 [hp_X]/1 mL; ACONITUM NAPELLUS 20 [hp_X]/1 mL; ANTIMONY POTASSIUM TARTRATE 20 [hp_X]/1 mL; ATROPA BELLADONNA 20 [hp_X]/1 mL; BRYONIA ALBA ROOT 20 [hp_X]/1 mL; PHENOL 20 [hp_X]/1 mL; COLCHICUM AUTUMNALE BULB 20 [hp_X]/1 mL; CONIUM MACULATUM FLOWERING TOP 20 [hp_X]/1 mL; IRON 20 [hp_X]/1 mL; GELSEMIUM SEMPERVIRENS ROOT 20 [hp_X]/1 mL; NITROGLYCERIN 20 [hp_X]/1 mL; HYOSCYAMUS NIGER 20 [hp_X]/1 mL; IPECAC 20 [hp_X]/1 mL; IRIS VERSICOLOR ROOT 20 [hp_X]/1 mL; LYCOPODIUM CLAVATUM SPORE 20 [hp_X]/1 mL; STRYCHNOS NUX-VOMICA SEED 20 [hp_X]/1 mL; KEROSENE 20 [hp_X]/1 mL; PHOSPHORUS 20 [hp_X]/1 mL; SEPIA OFFICINALIS JUICE 20 [hp_X]/1 mL; SYMPHORICARPOS ALBUS FRUIT 20 [hp_X]/1 mL; TOBACCO LEAF 20 [hp_X]/1 mL; THERIDION CURASSAVICUM 20 [hp_X]/1 mL; GINGER 20 [hp_X]/1 mL; ECHINACEA, UNSPECIFIED 11 [hp_X]/1 mL; HYPERICUM PERFORATUM 11 [hp_X]/1 mL; PASSIFLORA INCARNATA FLOWERING TOP 11 [hp_X]/1 mL; VALERIAN 11 [hp_X]/1 mL
INACTIVE INGREDIENTS: ALCOHOL; WATER

Dizzi-V 4779L

INDICATIONS & USAGE SECTION

Formulated for associated symptoms such as dizziness, nausea and sensations of motion, spinning or floating.

DOSAGE & ADMINISTRATION SECTION

Directions Ages 12 and up, take 6 drops by mouth (ages 0 to 11, give 3 drops) as needed or as directed by a health professional.

OTC - ACTIVE INGREDIENT SECTION

Equal parts of Echinacea 11x, Hypericum perforatum 11x, Passiflora incarnata 11x, Valeriana officinalis 11x, Absinthium 20x, Aconitum napellus 20x, Antimonium tartaricum 20x, Belladonna 20x, Bryonia 20x, Carbolicum acidum 20x, Colchicum autumnale 20x, Conium maculatum 20x, Ferrum metallicum 20x, Gelsemium sempervirens 20x, Glonoinum 20x, Hyoscyamus niger 20x, Ipecacuanha 20x, Iris versicolor 20x, Lycopodium clavatum 20x, Nux vomica 20x, Petroleum 20x, Phosphorus 20x, Sepia 20x, Symphoricarpus racemosus 20x, Tabacum 20x, Theridion 20x, Zingiber officinale 20x.

OTC - PURPOSE SECTION

Formulated for symptoms such as dizziness, nausea and sensations of motion, spinning or floating.

INACTIVE INGREDIENT SECTION

Inactive Ingredients: USP Purified Water; USP Gluten-free, non-GMO, organic cane alcohol 20%.

QUESTIONS SECTION

newtonlabs.net – Questions? 800.448.7256

Newton Laboratories, Inc. FDA Est # 1051203 - Conyers, GA 30013

WARNINGS SECTION

WARNINGS: Keep out of reach of children. Do not use if tamper-evident seal is broken or missing. If symptoms worsen or persist for more than a few days, consult a doctor. If pregnant or breast-feeding, ask a doctor before use.

OTC - PREGNANCY OR BREAST FEEDING SECTION

If pregnant or breast-feeding, ask a doctor before use.

OTC - KEEP OUT OF REACH OF CHILDREN SECTION

Keep out of reach of children.